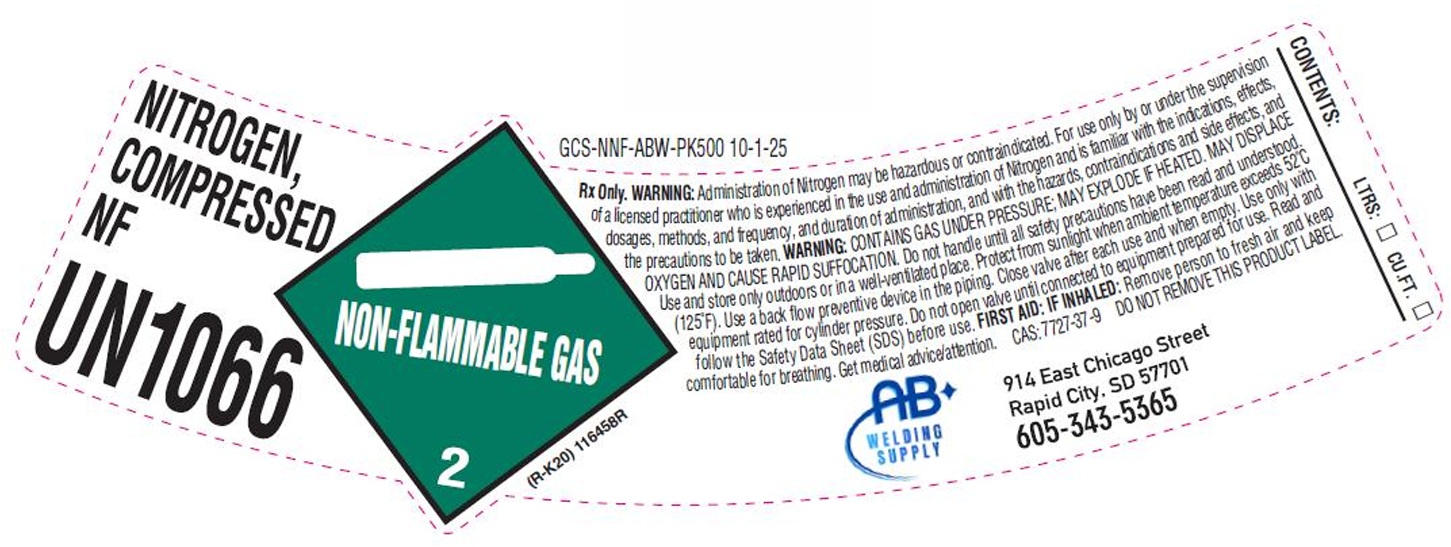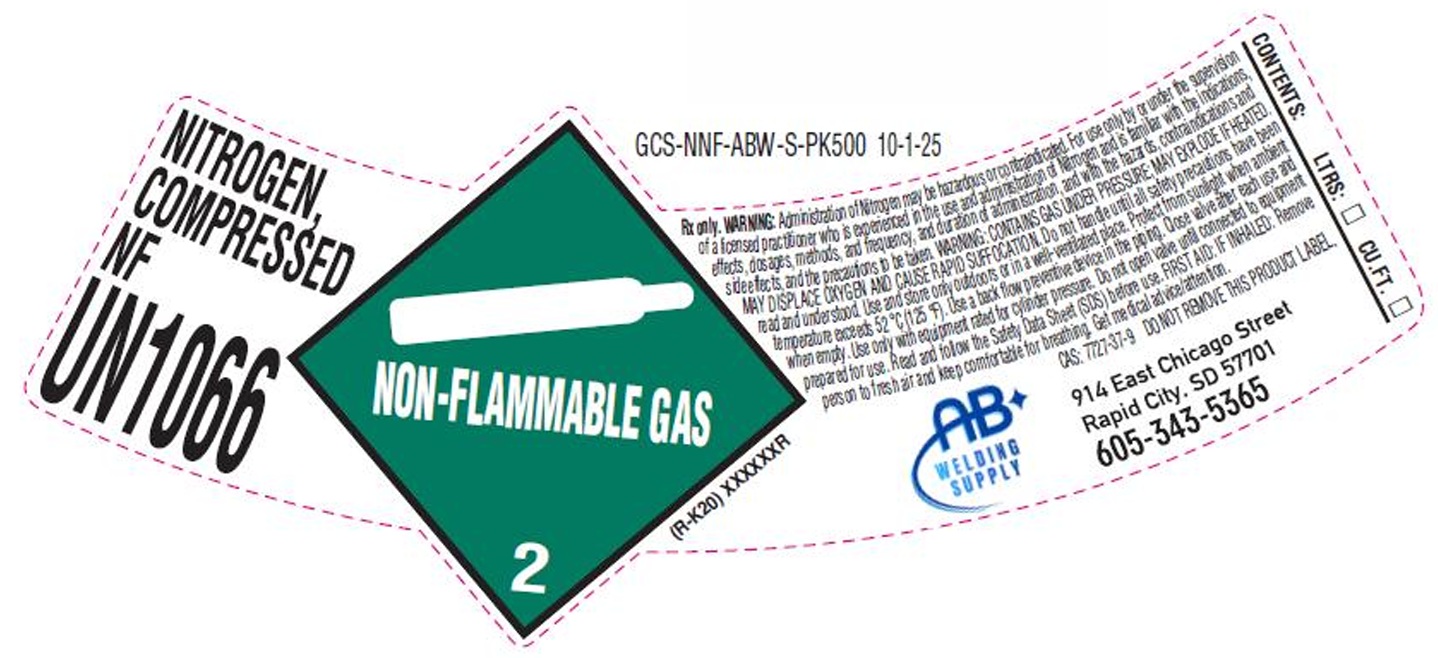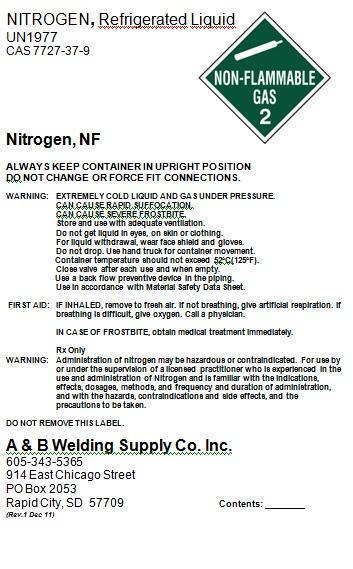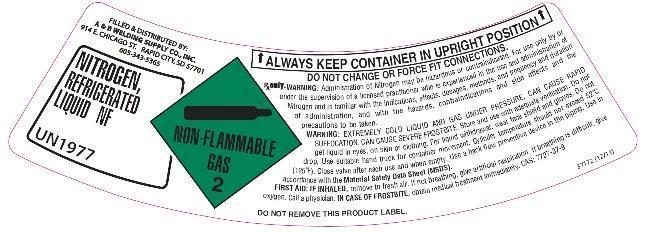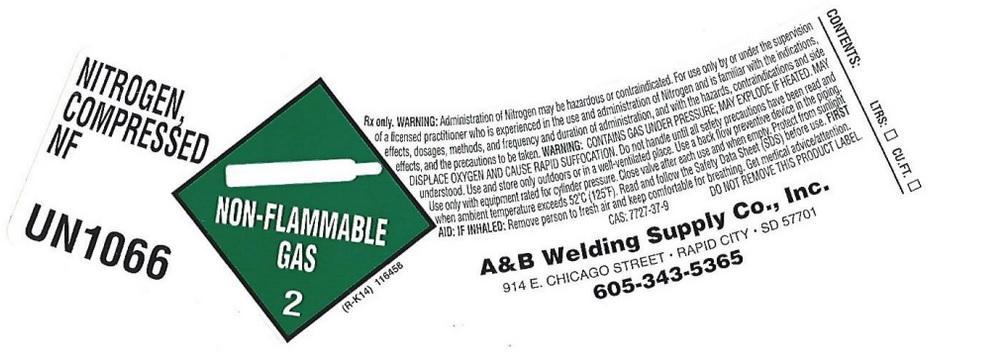 DRUG LABEL: Nitrogen
NDC: 55728-200 | Form: GAS
Manufacturer: A & B Welding Supply Co.
Category: prescription | Type: HUMAN PRESCRIPTION DRUG LABEL
Date: 20251118

ACTIVE INGREDIENTS: NITROGEN 990 mL/1 L

Nitrogen

PACKAGE LABEL

NITROGEN, Refrigerated Liquid
UN1977
CAS 7727-37-9
NON-FLAMMABLE GAS 2
Nitrogen, NF
ALWAYS KEEP CONTAINER IN UPRIGHT POSITION
DO NOT CHANGE OR FORCE FIT CONNECTIONS.
WARNING: EXTREMELY COLD LIQUID AND GAS UNDER PRESSURE.
CAN CAUSE RAPID SUFFOCATION.
CAN CAUSE SEVERE FROSTBITE.
Store and use with adequate ventilation.
Do not get liquid in eyes, on skin or clothing.
For liquid withdrawal, wear face shield and gloves.
Do not drop. Use hand truck for container movement.
Container temperature should not exceed 52oC(125oF).
Close valve after each use and when empty.
Use a back flow preventive device in the piping.
Use in accordance with Material Safety Data Sheet.
FIRST AID: IF INHALED, remove to fresh air. If not breathing, give artificial respiration. If breathing is difficult, give oxygen. Call a physician.
IN CASE OF FROSTBITE, obtain medical treatment immediately.
Rx Only
WARNING: Administration of nitrogen may be hazardous or contraindicated. For use by or under the supervision of a licensed practitioner who is experienced in the use and administration of Nitrogen and is familiar with the indications, effects, dosages, methods, and frequency and duration of administration, and with the hazards, contraindications and side effects, and the precautions to be taken.
DO NOT REMOVE THIS LABEL.
A and B Welding Supply Co. Inc.
605-343-5365
914 East Chicago Street
PO Box 2053
Rapid City, SD 57709 Contents:

PACKAGE LABEL

NITROGEN, COMPRESSED NF
UN 1066
NON-FLAMMABLE GAS 2
Rx only. WARNING: Administration of Nitrogen may be hazardous or contraindicated. For use only by or under the supervision of a licensed practitioner who is experienced in the use and administration of Nitrogen and is familiar with the indications, effects, dosages, methods, and frequency and duration of administration, and with the hazards, contraindications and side effects, and precautions to be taken. WARNING: CONTAINS GAS UNDER PRESSURE; MAY EXPLODE IF HEATED. MAY DISPLACE OXYGEN AND CAUSE RAPID SUFFOCATION. Do not handle until all safety precautions have been read and understood. Use and store only outdoors or in a well-ventilated place. Use a back flow preventive device in the piping. Use only with equipment rated for cylinder pressure. Close valve after each use and when empty. Protect from sunlight when ambient temperature exceed 52 degrees C (125 degrees F). Read and follow the Safety Data Sheet (SDS) before use. FIRST AID: IF INHALED: Remove person to fresh air and keep comfortable for breathing. Get medical advice/attention. CAS: 7727-37-9
DO NOT REMOVE THIS PRODUCT LABEL.
A&B Welding Supply Co., Inc.
914 W Chicago Street
Rapid City, SD 57701
605-343-5365
CONTENTS: LTRS CU FT

PACKAGE LABEL

FILLED AND DISTRIBUTED BY:

A AND B WELDING SUPPLY CO., INC

914 E CHICAGO ST

RAPID CITY, SD 57701

605-343-5365

NITROGEN, REFRIGERATED LIQUID NF

UN 1977

NON-FLAMMABLE GAS 2

ALWAYS KEEP CONTAINER IN UPRIGHT POSITION

DO NOT CHANGE OR FORCE FIT CONNECTIONS

Rx only. WARNING: Administration of Nitrogen my be hazardous or contraindicated. For use only by or under the supervision of a licensed practitioner who is experienced in the use and administration of Nitrogen and is familiar with the indications, effects, dosages, methods, and frequency and duration of administration, and with the hazards, contraindications and side effects and the precautions to be taken.

WARNING: EXTREMELY COLD LIQUID AND GAS UNDER PRESSURE. CAN CAUSE RAPID SUFFOCATION. CAN CAUSE SEVERE FROSTBITE. Store and use with adequate ventilation. Do not get liquid in eyes, on skin or clothing. For liquid withdrawal, wear face shield and gloves. Do not drop. Use suitable hand truck for container movement. cylinder temperature should not exceed 52 degrees C (125 degrees F). Close valve after each use and when empty. Use a back flow preventive device in the piping. Use in accordance with the Material Safety Data Sheet (MSDS).

FIRST AID: IF INHALED, remove to fresh air. If not breathing, give artificial respiration. If breathing is difficult, give Oxygen. Call a physician. IN CASE OF FROSTBITE, obtain medical treatment immediately. CAS 7727-37-9

PACKAGE LABEL

NITROGEN, COMPRESSED NF

UN1066

Rx Only. WARNING: Administration of Nitrogen may be hazardous or contraindicated. For use only by or under the supervision of a licensed practitioner who is experienced in the use and administration of Nitrogen and is familiar with the indications, effects, dosages, methods, and frequency, and duration of administration, and with the hazards, contraindications and side effects, and the precautions to be taken. WARNING: CONTAINS GAS UNDER PRESSURE; MAY EXPLODE IF HEATED. MAY DISPLACE OXYGEN AND CAUSE RAPID SUFFOCATION. Do not handle until all safety precautions have been read and understood. Use and store only outdoors or in a well-ventilated place. Protect from sunlight when ambient temperature exceeds 52 C (125 F). Use a back flow preventive device in the piping. Close valve after each use and when empty. Use only with equipment rated for cylinder pressure. Do not open valve until connected to equipment prepared for use. Read and follow the Safety Data Sheet (SDS) before use. FIRST AID: IF INHALED: Remove person to fresh air and keep comfortable for breathing. Get medical advice/attention. CAS: 7727-37-9 DO NOT REMOVE THIS PRODUCT LABEL.

AB WELDING SUPPLY

914 East Chicago Street

Rapid City, SD 57701

605-674-7523

NO SMOKING

NO VAPING

CONTENTS: LTRS: CU.FT.